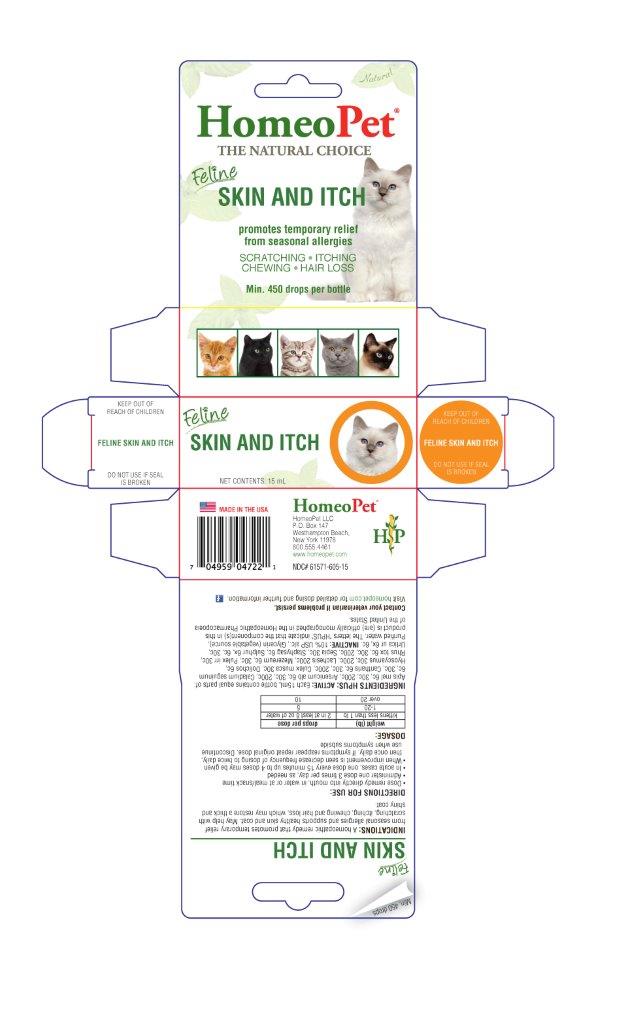 DRUG LABEL: Skin and Itch
NDC: 61571-605 | Form: LIQUID
Manufacturer: HomeoPet, LLC
Category: homeopathic | Type: OTC ANIMAL DRUG LABEL
Date: 20221130

ACTIVE INGREDIENTS: APIS MELLIFERA 6 [hp_C]/15 mL; ARSENIC TRIOXIDE 6 [hp_C]/15 mL; DIEFFENBACHIA SEGUINE 6 [hp_C]/15 mL; LYTTA VESICATORIA 6 [hp_C]/15 mL; CULEX PIPIENS 30 [hp_C]/15 mL; MUCUNA PRURIENS FRUIT TRICHOME 6 [hp_C]/15 mL; HYOSCYAMUS NIGER 30 [hp_C]/15 mL; LACHESIS MUTA VENOM 200 [hp_C]/15 mL; DAPHNE MEZEREUM BARK 6 [hp_C]/15 mL; PULEX IRRITANS 30 [hp_C]/15 mL; TOXICODENDRON PUBESCENS LEAF 6 [hp_C]/15 mL; SEPIA OFFICINALIS JUICE 30 [hp_C]/15 mL; DELPHINIUM STAPHISAGRIA SEED 6 [hp_C]/15 mL; SULFUR 6 [hp_X]/15 mL; URTICA DIOICA 6 [hp_X]/15 mL
INACTIVE INGREDIENTS: ALCOHOL; WATER; GLYCERIN

Feline Skin & Itch

Feline Skin & Itch

Promotes temporary relief from seasonal allergies

SCRATCHING - ITCHING - CHEWING - HAIR LOSS

Directions for Use and Dosage

- Dose remedy directly into mouth, in water or at meal/snack time
- Administer one dose 3 times per day, as needed
- In acute cases, one dose every 15 minutes up to 4 doses may be given
- When improvement is seen decrease frequency of dosing to twice daily, then once daily. If symptoms reappear repeat original dose. Discontinue use when symptoms subside

weight (lb) | drops per dose
kittens less than 1 lb | 2 in at least 8 oz of water
1-20 | 5
over 20 | 10

Contact Veterinarian

Contact Veterinarian if problems persist.

Visit homeopet.com for detailed dosing and further information.

INGREDIENTS HPUS: ACTIVE:

Apis mel 6c, 30c, 200c, Arsenicum alb 6c, 30c, 200c, Caladium seguinum 6c, 30c, Cantharis 6c, 30c, 200c, Culex musca 30c, Dolichos 6c, Hyoscyamus 30c, 200c, Lachesis 200c, Mezereum 6c, 30c, Pulex irr 30c, Rhus tox 6c, 30c, 200c, Sepia 30c, Staphysag 6c, Sulphur 6x, 6c, 30c, Uritica ur 6x, 6c.

INACTIVE INGREDIENTS

USP Alcohol, Purified Water

INDICATIONS

A natural homeopathic remedy that promotes temporary relief from constant scratching, itching, gnawing, hair loss and bald belly caused by allergies. Helps to detoxify the skin from the inside, leaving the coat thick and shiny.

PACKAGE LABEL

Add image transcription here...